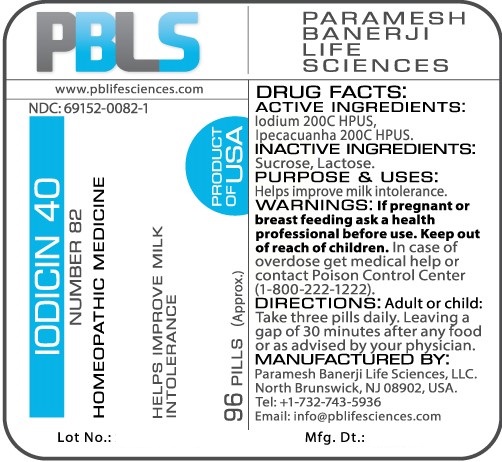 DRUG LABEL: Iodicin 40 Number 82
NDC: 69152-0082 | Form: PELLET
Manufacturer: Paramesh Banerji Life Sciences LLC
Category: homeopathic | Type: HUMAN OTC DRUG LABEL
Date: 20170215

ACTIVE INGREDIENTS: IODINE 200 [hp_C]/1 1; IPECAC 200 [hp_C]/1 1
INACTIVE INGREDIENTS: LACTOSE; SUCROSE

DRUG FACTS: Active Ingredients

Iodium 200C HPUS, Ipecacuanha 200C HPUS

Inactive Ingredients

Sucrose, Lactose

Purpose

Helps improve milk intolerance

Uses

Helps improve milk intolerance

Warnings

If pregnant or breast feeding ask a health professional before use.

Keep out of reach of children. In case of overdose, get medical help or contact a Poison Control Center (1-800-222-1222) right away.

Direction

Adult or child: Take three pills daily. Leaving a gap of 30 minutes after any food or as advised by your physician.

Manufactured by

Paramesh Banerji Life Sciences, LLC.

North Brunswick, NJ 08902, USA.

Tel: +1-732-743-5936

Email: info@pblifesciences.com

Principal Display Panel

NDC: 69152-0082-1

Iodicin 40

Number 82

Homeopathic Medicine

Helps improve milk intolerance

96 pills (Approx.)

Product of USA